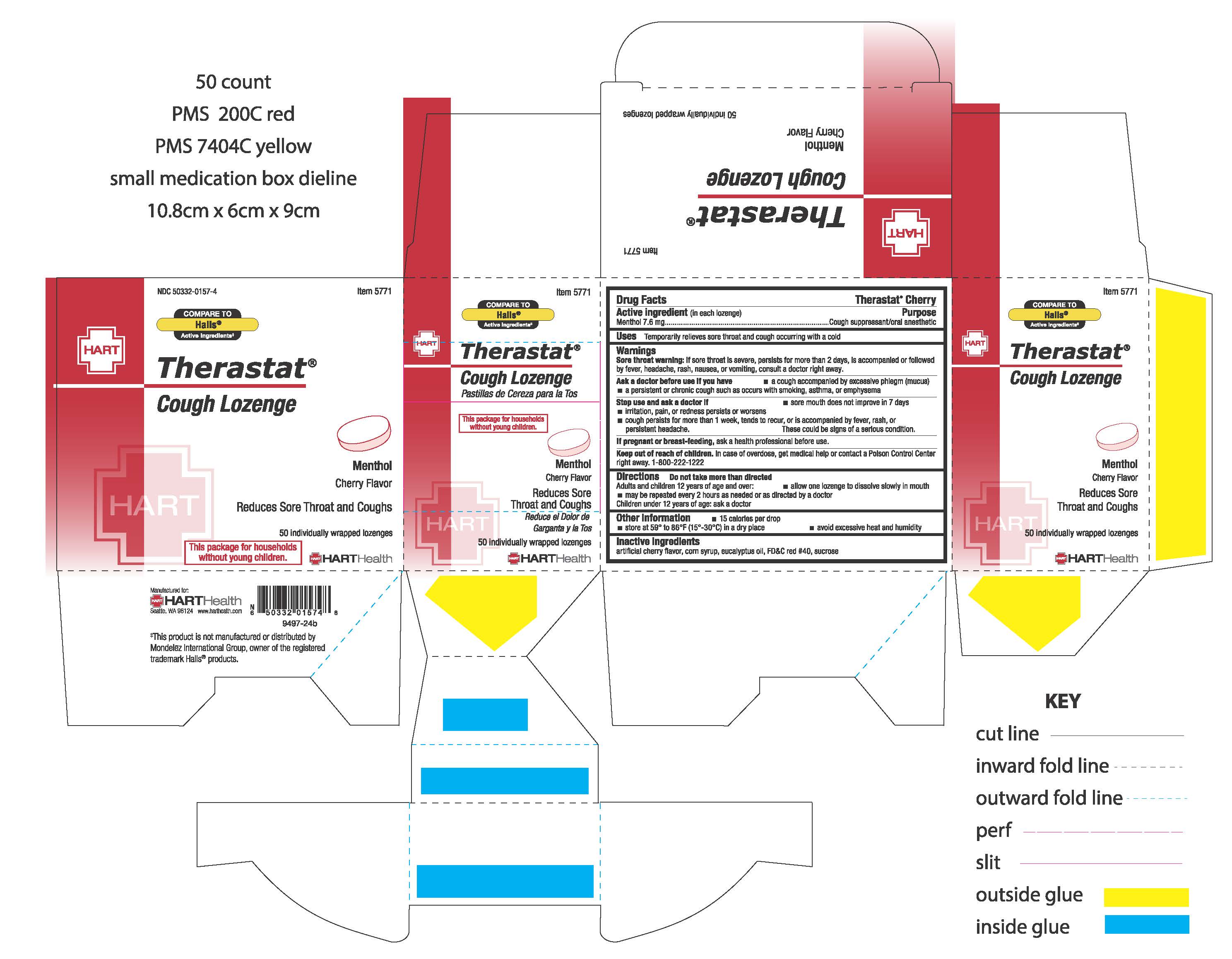 DRUG LABEL: THERASTAT, CHERRY
NDC: 50332-0157 | Form: LOZENGE
Manufacturer: HART Health
Category: otc | Type: HUMAN OTC DRUG LABEL
Date: 20251223

ACTIVE INGREDIENTS: MENTHOL 7.6 mg/1 1
INACTIVE INGREDIENTS: CORN SYRUP; EUCALYPTUS OIL; FD&C RED NO. 40; SUCROSE

THERASTAT, CHERRY

Active ingredient (in each lozenge)

Menthol 7.6 mg

Purpose

Cough suppressant/oral anesthetic

Uses

Temporarily relieves sore throat and cough occurring with a cold

Warnings

Sore throat warning: If sore throat is severe, persists for more than 2 days, is accompanied or followed by fever, headache, rash, nausea, or vomiting, consult a doctor right away

Ask a doctor before use if you have

- a cough acccompanied by excessive phlegm (mucus)
- a persistent or chronic cough such as occurs with smoking, asthma, or emphysema

Stop use and ask a doctor if:

- sore mouth does improve in 7 days
- irritation, pain or redness persists or worsens
- cough persists for more than 1 week, tends to recur, or is accompanied by fever, rash, or persistent headache

These could be signs of a serious condition

PREGNANCY OR BREAST FEEDING

If pregnant or breast-feeding, ask a health professional before use.

Keep out of reach of children. In case of overdose, get medical help or contact a Poison Control Center right away. 1-800-222-1222

Directions

Do not take more than directed

Adults and children 12 years of age and over:

- allow one lozenge to dissolve slowly in mouth
- may be repeated every 2 hours as needed or as directed by a doctor

Children under 12 years of age: ask a doctor

Other information

- 15 calories per drop
- store at 59° to 86° F (15° t-30°C) in a dry place
- avoid excessive heat and humidity

Inactive ingredients

artificial cherry flavor, corn syrup, eucalyptus oil, FD&C red #40, sucrose